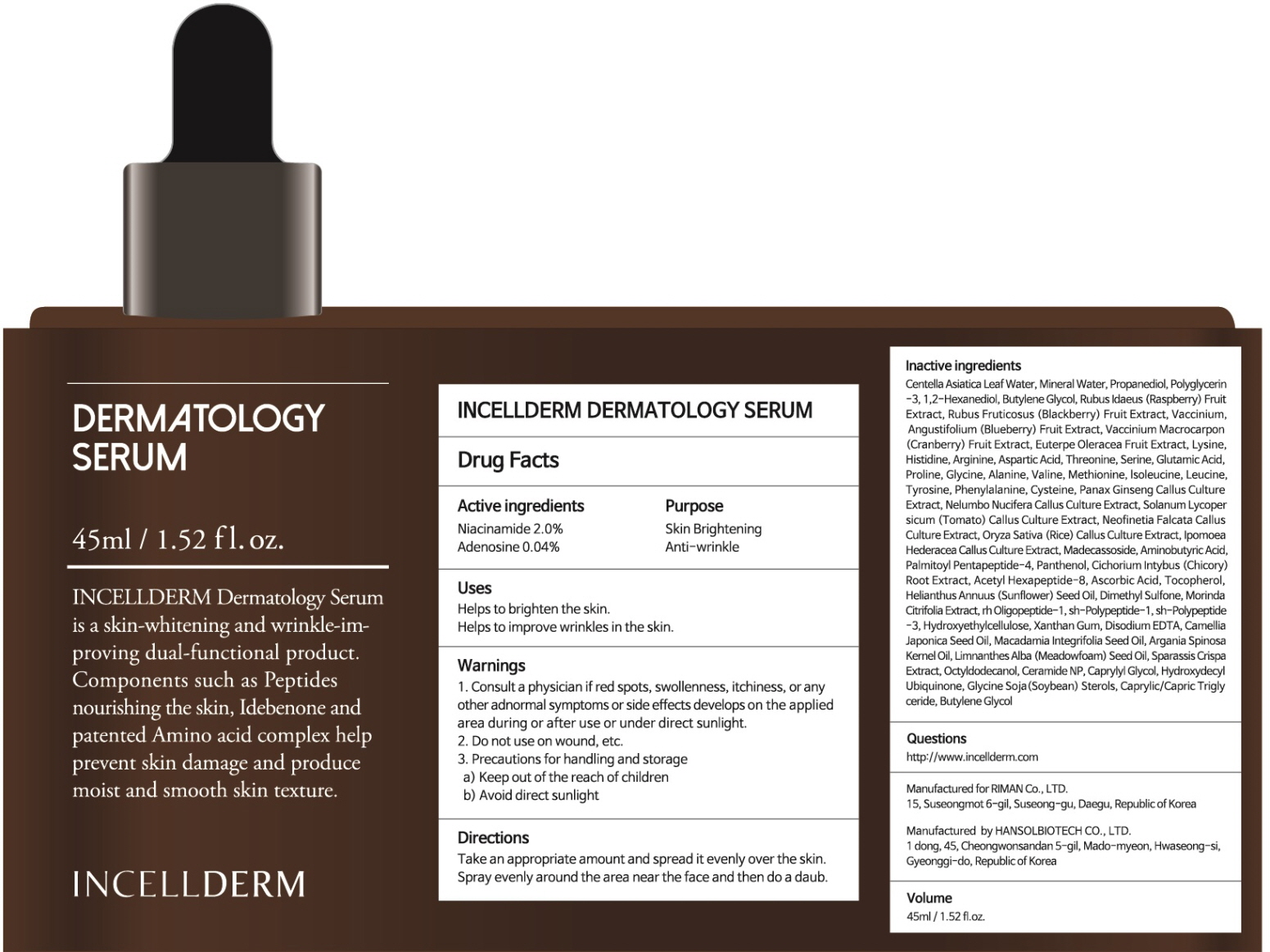 DRUG LABEL: INCELLDERM DERMATOLOGY SERUM
NDC: 72650-030 | Form: LIQUID
Manufacturer: Riman Co., Ltd.
Category: otc | Type: HUMAN OTC DRUG LABEL
Date: 20190419

ACTIVE INGREDIENTS: Niacinamide 0.90 g/45 mL; Adenosine 0.01 g/45 mL
INACTIVE INGREDIENTS: CENTELLA ASIATICA LEAF; WATER

ACTIVE INGREDIENT

Active ingredients: Niacinamide 2.0%, Adenosine 0.04%

INACTIVE INGREDIENT

Inactive ingredients:
Centella Asiatica Leaf Water, Mineral Water, Propanediol, Polyglycerin-3, 1,2-Hexanediol, Butylene Glycol, Rubus Idaeus (Raspberry) Fruit Extract, Rubus Fruticosus (Blackberry) Fruit Extract, Vaccinium, Angustifolium (Blueberry) Fruit Extract, Vaccinium Macrocarpon (Cranberry) Fruit Extract, Euterpe Oleracea Fruit Extract, Lysine, Histidine, Arginine, Aspartic Acid, Threonine, Serine, Glutamic Acid, Proline, Glycine, Alanine, Valine, Methionine, lsoleucine, Leucine, Tyrosine, Phenylalanine, Cysteine, Panax Ginseng Callus Culture Extract, Nelumbo Nucifera Callus Culture Extract, Solanum Lycopersicum (Tomato) Callus Culture Extract, Neofinetia Falcata Callus Culture Extract, Oryza Sativa (Rice) Callus Culture Extract, Ipomoea Hederacea Callus Culture Extract, Madecassoside, Aminobutyric Acid, Palmitoyl Pentapeptide-4, Panthenol, Cichorium Intybus (Chicory) Root Extract , Acetyl Hexapeptide-8, Ascorbic Acid, Tocopherol, Helianthus Annuus (Sunflower) Seed Oil, Dimethyl Sulfone, Morinda Citrifolia Extract, rh-Oligopeptide-1, sh-Polypeptide-1, sh-Polypeptide-3, Hydroxyethylcellulose, Xanthan Gum, Disodium EDTA, Camellia Japonica Seed Oil, Macadamia Integrifolia Seed Oil, Argania Spinosa Kernel Oil, Limnanthes Alba (Meadowfoam) Seed Oil, Sparassis Crispa Extract, Octyldodecanol, Ceramide NP, Caprylyl Glycol, Hydroxydecyl Ubiquinone, Glycine Soja(Soybean) Sterols, Caprylic/Capric Triglyceride, Butylene Glycol

PURPOSE

Purpose: Skin Brightening, Anti-wrinkle

WARNINGS

1. Consult a physician if red spots, swollenness, itchiness, or any other adnormal symptoms or side effects develops on the applied area during or after use or under direct sunlight.
2. Do not use on wound, etc.
3. Precautions for handling and storage
a) Keep out of the reach of children
b) Avoid direct sunlight

KEEP OUT OF REACH OF CHILDREN

Uses

Helps to brighten the skin.
Helps to improve wrinkles in the skin.

Directions

Take an appropriate amount and spread it evenly over the skin.
Please put the appropriate amount on the skin and wait (daub).